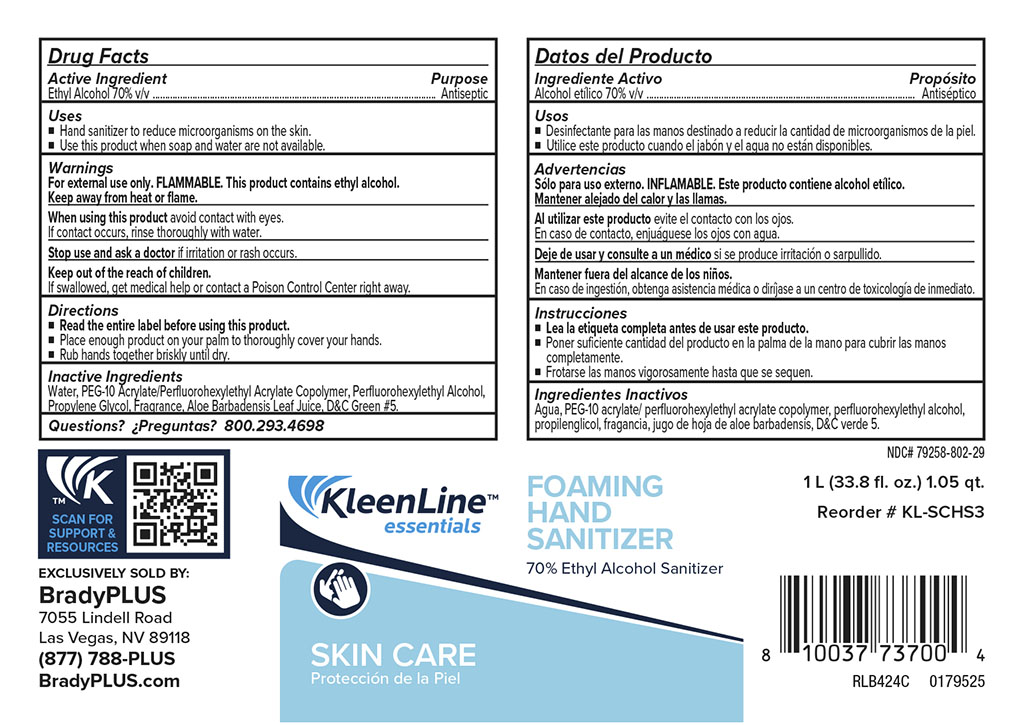 DRUG LABEL: KleenLine Essentials Foaming Hand Sanitizer
NDC: 79258-802 | Form: LIQUID
Manufacturer: Brady Industries
Category: otc | Type: HUMAN OTC DRUG LABEL
Date: 20241216

ACTIVE INGREDIENTS: ALCOHOL 0.7 mL/1 mL
INACTIVE INGREDIENTS: PEG-10 ACRYLATE/PERFLUOROHEXYLETHYL ACRYLATE COPOLYMER; TETRAHYDROLINALYL ACETATE; 4-CYCLOHEXYL-2-METHYL-2-BUTANOL; WATER; HYDROXYCITRONELLAL; ALOE BARBADENSIS LEAF JUICE; TETRAHYDROLINALOOL; 2-SEC-BUTYL CYCLOHEXANONE; D&C GREEN NO. 5; EBANOL; 2-(PERFLUOROHEXYL)ETHANETHIOL; BIS-PEG-12 DIMETHICONE (70 MPA.S); PROPYLENE GLYCOL; HEXYL ACETATE

KleenLine Essentials Foaming Hand Sanitizer

INACTIVE INGREDIENT

Water, PEG-10 Acrylate/Perfluorohexylethyl/acrylate polymer, Perfluorohexyl Alcohol, Propylene Glycol, Fragrance, Aloe Barbadensis Leaf Juice, D&C Green 5,

INSTRUCTIONS FOR USE

Read entire label before using this product

Place enough product on your palm to thoroughly cover your hands

Rub hands together briskly until dry

ACTIVE INGREDIENT

Ethyl Alcohol

Keep out of reach of children

if swalllowed cget medical help or contact Poison Control Center righ away

PURPOSE

Antiseptic

WARNINGS

For external use only. FLAMMABLE. This product contains ethyl alcohol. Keep away from heat or flame

usage

Hand sanitizer to reduce microorganisms on skin

Use this product when soap and water are not available

DOSAGE AND ADMINISTRATION

Place enough product on your palms to thoroughly cover hands

rub hands together briskly until dry